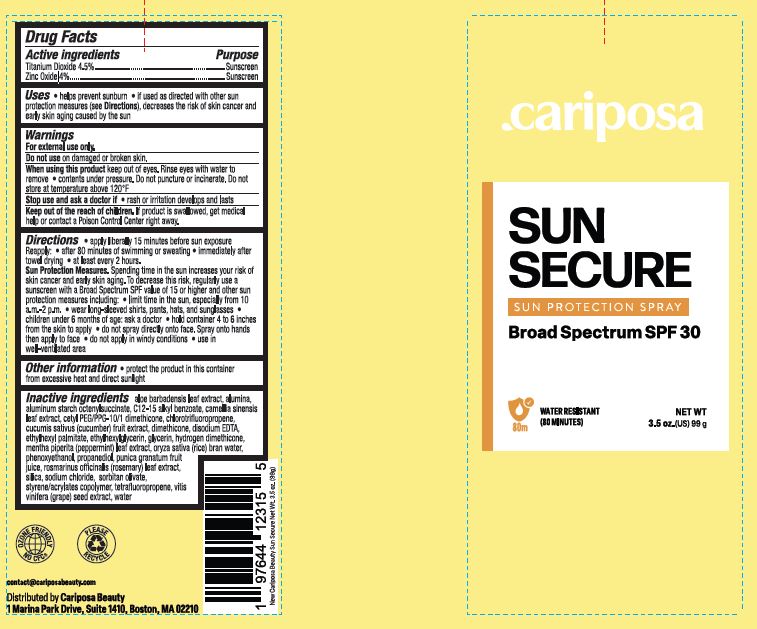 DRUG LABEL: SPF30 Sunscreen

NDC: 84267-003 | Form: SPRAY
Manufacturer: Talent Brands Company LLC
Category: otc | Type: HUMAN OTC DRUG LABEL
Date: 20240418

ACTIVE INGREDIENTS: TITANIUM DIOXIDE 4.5 g/100 g; ZINC OXIDE 4 g/100 g
INACTIVE INGREDIENTS: ALOE; ALUMINUM OXIDE; ALUMINUM STARCH OCTENYLSUCCINATE; ALKYL (C12-15) BENZOATE; CAMELLIA SINENSIS FLOWER; CETYL PEG/PPG-10/1 DIMETHICONE (HLB 2); CUCUMIS SATIVUS LEAF; DIMETHICONE; EDETATE DISODIUM; ETHYLHEXYL PALMITATE; ETHYLHEXYLGLYCERIN; GLYCERIN; HYDROGEN DIMETHICONE (13 CST); MENTHA PIPERITA; RICE BRAN, DEFATTED; PHENOXYETHANOL; PROPANEDIOL; POMEGRANATE JUICE; ROSMARINUS OFFICINALIS WHOLE; SILICON DIOXIDE; SODIUM CHLORIDE; SORBITAN OLIVATE; STYRENE/ACRYLAMIDE COPOLYMER (500000 MW); GRAPE; WATER

SPF30 Mineral Spray

Active ingredients Purpose

Titanium Dioxide 4.5% Sunscreen

Zinc Oxide 4% Sunscreen

Uses

•helps prevent sunburn• If used as directed with other sun protection measures (see Oirections),decreases the risk of skin cancer and early skin aging caused by the sun.

Do not use on

• damaged or broken skin.

When using this product

- keep out of eyes. Rinse with waterto remove.
- contents under pressure.
- do not puncture or incinerate
- do not syore at temperature above 120F

Stop use and ask a doctor if

• rash or initation develops and lasts

Directions:

- apply liberally 15 minutes before sun exposure and as needed. Reapply:
- after 80 minutes of sweeming or sweating
- immidiately after towel drying
- at least every 2 hours
- Sun Protection Measures. Spending time in the sun increase your risk of skin cancer and early skin aging. To decrease this risk. regularly usea sunscreen wrtha Broad Spectrum SPF value of15 or higher and other suncrin protection measures including:
- limrt time in the sun, especial from 10a.m. -2 p.rn.•wear long-sleeve shorts , pants, hats and sunglasses
- children under 6 months of age: ask a doctor

Other information

Protect the product in this container from excessive heat and direct sun

Inactive ingredients

ALOE
ALUMINA
ALUMINUM STARCH OCTENYLSUCCINATE
ALKYL (C12-15) BENZOATE
CAMELLIA SINENSIS FLOWER EXTRACT
CETYL PEG/PPG-10/1 DIMETHICONE
CUCUMIS SATIVUS FRUET EXTRACT
DIMETHICONE
EDETATE DISODIUM
ETHYLHEXYL PALMITATE
ETHYLHEXYLGLYCERIN
GLYCERIN
HYDROGEN DIMETHICONE
MENTHA PIPERITA (UNII: 79M2M2UDA9)
RICE BRAN, DEFATTED
PHENOXYETHANOL
PROPANEDIOL
POMEGRANATE JUICE
ROSMARINUS OFFICINALIS LEAF EXTRACT
SILICON DIOXIDE
SODIUM CHLORIDE
SORBITAN OLIVATE
STYRENE/ACRYLAMIDE COPOLYMER
GRAPE SEED EXTRACT
WATER